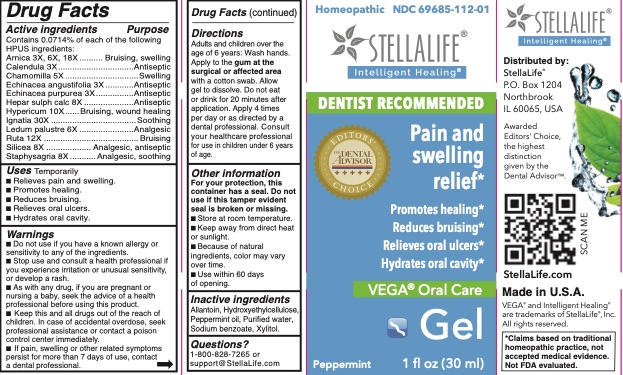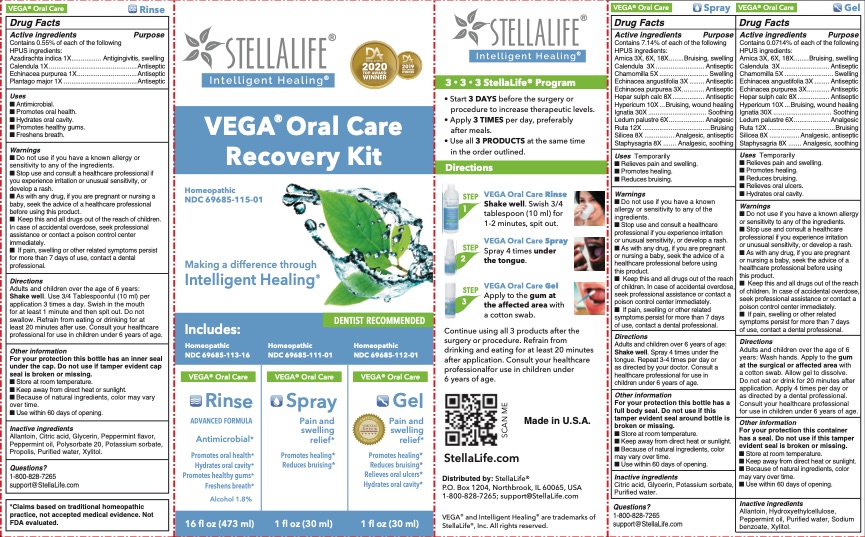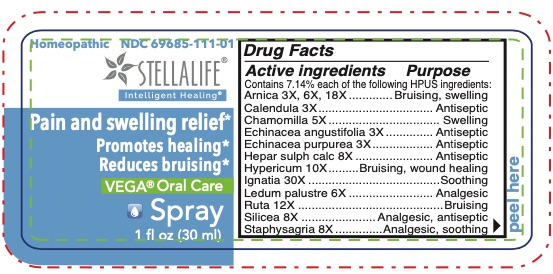 DRUG LABEL: StellaLife VEGA Oral Care Gel
NDC: 69685-112 | Form: GEL
Manufacturer: StellaLife, Inc.
Category: homeopathic | Type: HUMAN OTC DRUG LABEL
Date: 20251224

ACTIVE INGREDIENTS: LEDUM PALUSTRE TWIG 6 [hp_X]/1 mL; CALENDULA OFFICINALIS FLOWERING TOP 3 [hp_X]/1 mL; ECHINACEA ANGUSTIFOLIA 3 [hp_X]/1 mL; HYPERICUM PERFORATUM 10 [hp_X]/1 mL; STRYCHNOS IGNATII SEED 30 [hp_X]/1 mL; SILICON DIOXIDE 8 [hp_X]/1 mL; RUTA GRAVEOLENS FLOWERING TOP 12 [hp_X]/1 mL; ARNICA MONTANA 18 [hp_X]/1 mL; MATRICARIA RECUTITA 5 [hp_X]/1 mL; ECHINACEA PURPUREA 3 [hp_X]/1 mL; DELPHINIUM STAPHISAGRIA SEED 8 [hp_X]/1 mL; CALCIUM SULFIDE 8 [hp_X]/1 mL
INACTIVE INGREDIENTS: PEPPERMINT OIL; HYDROXYETHYL CELLULOSE (100 MPA.S AT 2%); WATER; SODIUM BENZOATE; XYLITOL; ALLANTOIN

StellaLife VEGA Oral Care Spray

Uses

Temporarily

- Relieves pain and swelling.
- Promotes healing.
- Reduces bruising.

Usage

Temporarily

- Relieves pain and swelling.
- Promotes healing.
- Reduces bruising.

Warnings

Do not use if you have a known allergy or sensitivity to any of the following ingredients

Stop use and consult a healthcare professional if you experience irritation or unusual sensitivity, or develop a rash.
As with any drug, if you are pregnant or nursing a baby, seek the advice of a healthcare professional before using this product.
Keep this and all drugs out of the reach of children. In case of accidental overdose, seek professional assistance or contact poison control center immediately.
If pain, swelling or other related symptoms persist for more than 7 days of use, contact a dental professional.

Keep Out of Reach of Children

Keep this and all drugs out of reach of children. In case of accidental overdose, seek professional assistance or contact a poison control center immediately.

Directions

Adults and children over 6 years of age: Shake well. Spray 4 times per application under the tongue. Repeat 3-4 times per day or as directed by your doctor. Consult a healthcare professional for use in children under 6 years of age.

Other Information

For your protection, this bottle has a full body seal. Do not use if this tamper evident seal is broken or missing.

Store at room temperature.
Keep away from direct heat or sunlight.
Because of natural ingredients, color may vary over time.
Use within 60 days of opening.

Inactive Ingredients

Citric acid, Glycerin, Potassium sorbate, Purified water.

Drug Facts

Contains 7.14% of each of the following HPUS ingredients:

Active Ingredients | Purpose
Arnica 3X, 6X, 18X | Bruising, swelling
Calendula 3X | Antiseptic
Chamomilla 5X | Swelling
Echinacea angustifolia 3X | Antiseptic
Echinacea purpurea 3X | Antiseptic
Hepar sulph calc 8X | Antiseptic
Hypericum 10X | Bruising, would healing
Ignata 30X | Soothing
Ledum palustre 6X | Analgesic
Ruta 12X | Bruising
Silicea 8X | Analgesic, antiseptic
Staphysagria 8X | Analgesic, soothing

StellaLife VEGA Oral Care Gel

Drug Facts

Contains 0.0714% of each of the following HPUS ingredients:

Active Ingredients | Purpose
Arnica 3X, 6X, 18X | Bruising, swelling
Calendula 3X | Antiseptic
Chamomilla 5X | Swelling
Echinacea angustifolia 3X | Antiseptic
Echinacea purpurea 3X | Antiseptic
Hepar sulph calc 8X | Antiseptic
Hypericum 10X | Bruising, would healing
Ignata 30X | Soothing
Ledum palustre 6X | Analgesic
Ruta 12X | Bruising
Silicea 8X | Analgesic, antiseptic
Staphysagria 8X | Analgesic, soothing

Uses

- Promotes oral health
- Hydrates oral cavity
- Supports healthy gums
- Freshens breath

Usage

Temporarily

- Relieves pain and swelling.
- Promotes healing.
- Reduces bruising.
- Relieves oral ulcers.
- Hydrates oral cavity.

Warnings

Do not use if you have a known allergy or sensitivity to any of the following ingredients
Stop use and consult a healthcare professional if you experience irritation or unusual sensitivity, or develop a rash.
As with any drug, if you are pregnant or nursing a baby, seek the advise of a healthcare professional before using this product.
Keep this and all drugs out of the reach of children. In case of accidental overdose, seek professional assistance or contact poison control center immediately.
If pain, swelling or other related symptoms persist for more than 7 days of use, contact a dental professional.

Keep Out of Reach of Children

Keep this and all drugs out of reach of children. In case of accidental overdose, seek professional assistance or contact a poison control center immediately.

Directions

Adults and children over the age of 6 years: Wash hands. Apply to the gum at the surgical or affected area with a cotton swab. Allow gel to dissolve. Do not eat or drink for 20 minutes after application. Apply 4 times per day or as directed by a dental professional. Consult your healthcare professional for use in children under 6 years of age.

Other Information

For your protection, this bottle has a full body seal. Do not use if this tamper evident seal is broken or missing.

Store at room temperature.
Keep away from direct heat or sunlight.
Because of natural ingredients, color may vary over time.
Use within 60 days of opening.

Inactive Ingredients

Allantoin, Hydroxyethylcellulose, Peppermint oil, Purified water, Sodium benzoate, Xylitol.

StellaLife VEGA Oral Care Rinse (Peppermint)

Drug Facts

Contains 0.55% of each of the following HPUS ingredients:

Active Ingredients | Purpose
Azadirachta Indica 1X | Antiginivitis, swelling
Calendula 1X | Antiseptic
Echinacea Purpurea 1X | Antiseptic
Plantago Major 1X | Antiseptic

Uses

- Promotes oral health
- Hydrates oral cavity
- Supports healthy gums
- Freshens breath

Usage

- Antimicrobial
- Promotes oral health
- Hydrates oral cavity
- Supports healthy gums
- Freshens breath

Warnings

Do not use if you have a known allergy or sensitivity to any of the following ingredients
Stop use and consult a healthcare professional if you experience irritation or unusual sensitivity, or develop a rash.
As with any drug, if you are pregnant or nursing a baby, seek the advise of a healthcare professional before using this product.
Keep this and all drugs out of the reach of children. In case of accidental overdose, seek professional assistance or contact poison control center immediately.
If pain, swelling or other related symptoms persist for more than 7 days of use, contact a dental professional.

Keep Out of Reach of Children

Keep this and all drugs out of reach of children. In case of accidental overdose, seek professional assistance or contact a poison control center immediately.

Directions

Adults and children over the age of 6 years: Shake well. Use 3/4 tablespoon (10 ml) per application 3 times a day. Swish in the mouth for 1-2 minutes and then spit out. Do not swallow. Refrain from eating or drinking for at least 20 minutes after use. Consult your healthcare professional for use in children under 6 years of age.

Other Information

For your protection, this bottle has a full body seal. Do not use if this tamper evident seal is broken or missing.

Store at room temperature.
Keep away from direct heat or sunlight.
Because of natural ingredients, color may vary over time.
Use within 60 days of opening.

Inactive Ingredients

Allantoin, Citric acid, Glycerin, Peppermint flavor, Peppermint oil, Polysorbate 20, Potassium sorbate, Propolis, Purified water, Xylitol